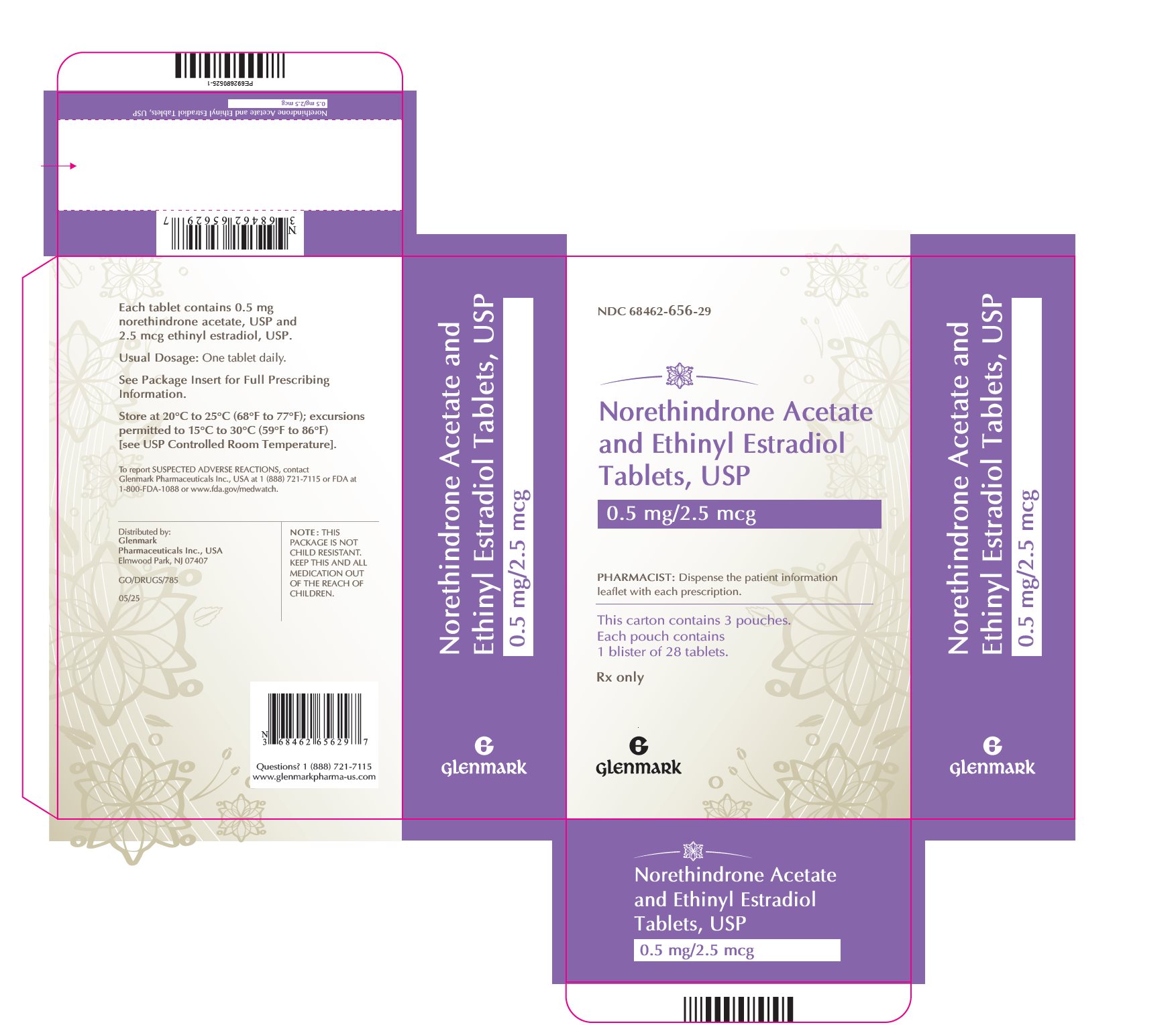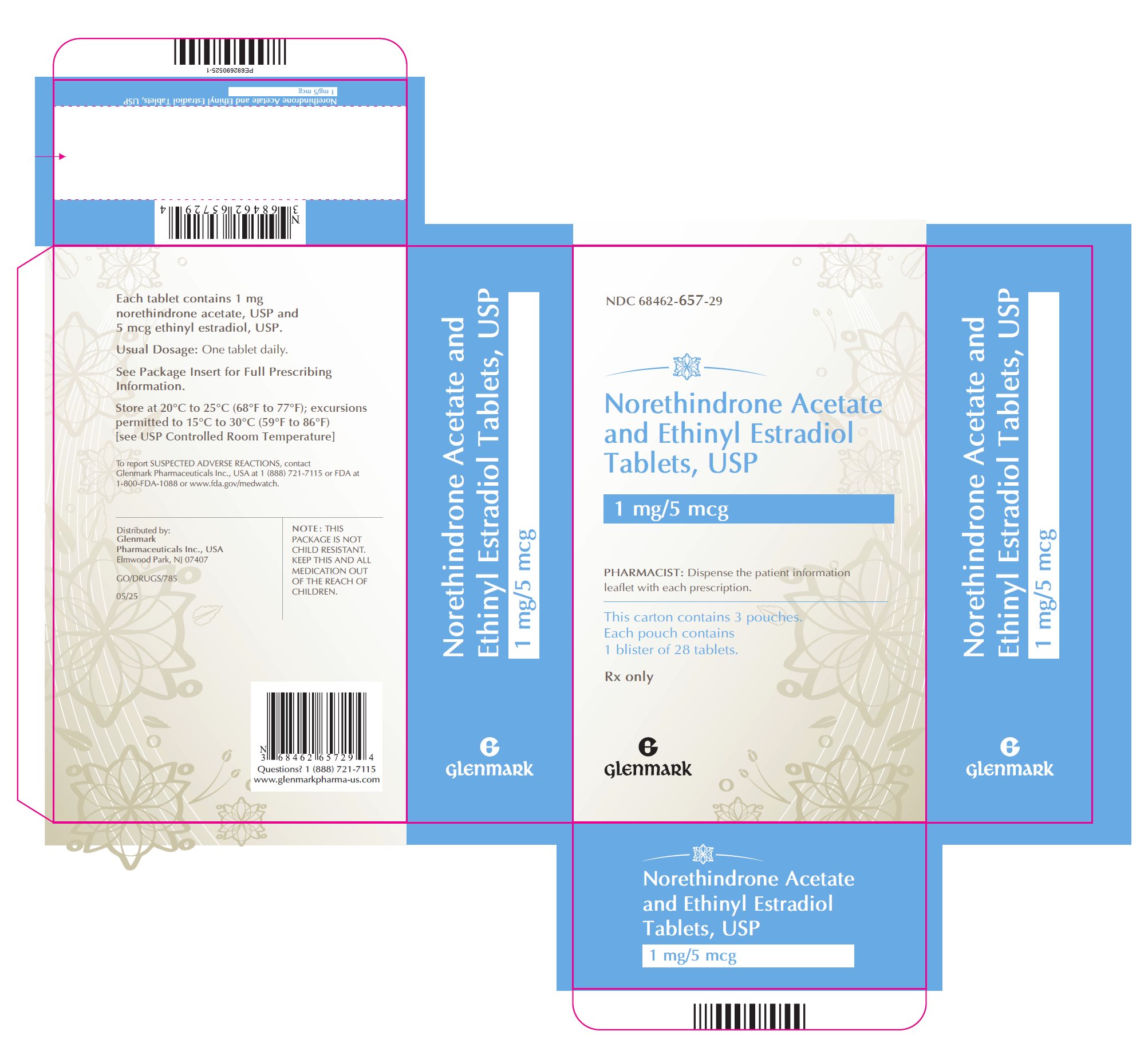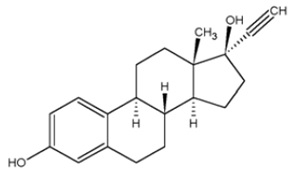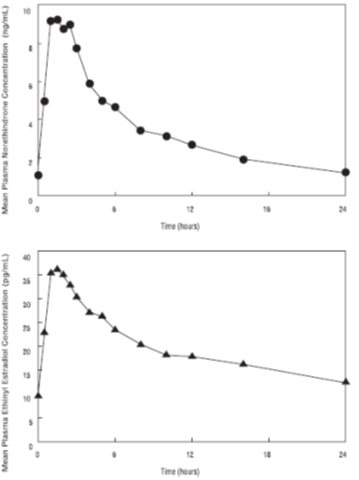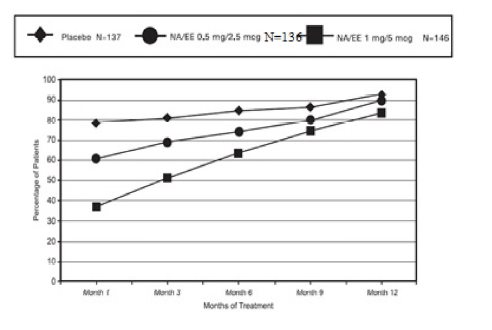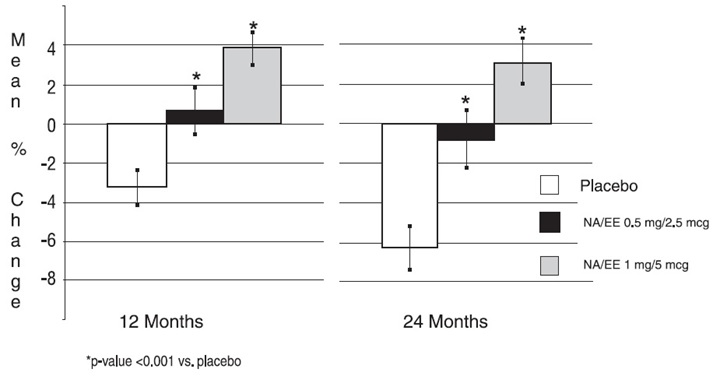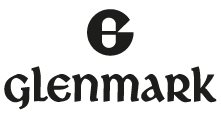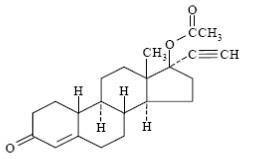 DRUG LABEL: Norethindrone Acetate and Ethinyl Estradiol
NDC: 68462-656 | Form: TABLET
Manufacturer: Glenmark Pharmaceuticals Inc., USA
Category: prescription | Type: HUMAN PRESCRIPTION DRUG LABEL
Date: 20260129

ACTIVE INGREDIENTS: NORETHINDRONE ACETATE 0.5 mg/1 1; ETHINYL ESTRADIOL 2.5 ug/1 1
INACTIVE INGREDIENTS: CALCIUM STEARATE; STARCH, CORN; ISOPROPYL ALCOHOL; LACTOSE MONOHYDRATE; MICROCRYSTALLINE CELLULOSE; POVIDONE K30; .ALPHA.-TOCOPHEROL; D&C RED NO. 30; TALC

HIGHLIGHTS OF PRESCRIBING INFORMATION

These highlights do not include all the information needed to use NORETHINDRONE ACETATE AND ETHINYL ESTRADIOL safely and effectively. See full prescribing information for NORETHINDRONE ACETATE AND ETHINYL ESTRADIOL.
NORETHINDRONE ACETATE and ETHINYL ESTRADIOL tablets, for oral use
Initial U.S. Approval: 1968

WARNING: CARDIOVASCULAR DISORDERS, PROBABLE DEMENTIA, BREAST CANCER, and ENDOMETRIAL CANCER

See full prescribing information for complete boxed warning.

Estrogen Plus Progestin Therapy

- The Women’s Health Initiative (WHI) estrogen plus progestin substudy reported increased risks of pulmonary embolism (PE), deep vein thrombosis (DVT), stroke, and myocardial infarction (MI) (5.1)
- The WHI estrogen plus progestin substudy reported increased risk of invasive breast cancer (5.2)
- The WHI Memory Study (WHIMS) estrogen plus progestin ancillary study of WHI reported an increased risk of probable dementia in postmenopausal women 65 years of age and older (5.3)
- Do not use estrogen plus progestogen therapy for the prevention of cardiovascular disease of dementia (5.1, 5.3)

Estrogen-Alone Therapy

- There is an increased risk of endometrial cancer in a woman with a uterus who uses unopposed estrogens (5.2)
- The WHI estrogen-alone substudy reported increased risks of stroke and DVT (5.1)
- The WHIMS estrogen-alone ancillary study of WHI reported an increased risk of probable dementia in postmenopausal women 65 years of age and older (5.3)
- Do not use estrogen-alone therapy for the prevention of cardiovascular disease or dementia (5.1, 5.3)

RECENT MAJOR CHANGES

Boxed Warning 5/2023

Warnings and Precautions, Malignant Neoplasms (5.2) 11/2023

1 INDICATIONS AND USAGE

Norethindrone acetate and ethinyl estradiol tablets are a combination of an estrogen and progestin indicated in a woman with a uterus for:

- Treatment of Moderate to Severe Vasomotor Symptoms due to Menopause (1.1)
- Prevention of Postmenopausal Osteoporosis (1.2)

2 DOSAGE AND ADMINISTRATION

- One tablet orally once daily (2.1, 2.2)

3 DOSAGE FORMS AND STRENGTHS

- Round, light pink to light tablet contains 0.5 mg norethindrone acetate and 2.5 mcg ethinyl estradiol (3)
- Round, white to off-white tablet contains 1 mg norethindrone acetate and 5 mcg ethinyl estradiol (3)

4 CONTRAINDICATIONS

- Undiagnosed abnormal genital bleeding (4, 5.2)
- Breast cancer or a history of breast cancer (4, 5.2)
- Estrogen-dependent neoplasia (4, 5.2)
- Active DVT, PE, or history of these conditions (4, 5.1)
- Active arterial thromboembolic disease (for example, stroke and MI), or a history of these conditions (4, 5.1)
- Known anaphylactic reaction, angioedema or hypersensitivity to norethindrone acetate and ethinyl estradiol tablets (4)
- Hepatic impairment or disease (4, 5.10)
- Protein C, protein S, or antithrombin deficiency, or other known thrombophilic disorders (4)

5 WARNINGS AND PRECAUTIONS

- Estrogens increase the risk of gallbladder disease (5.4)
- Discontinue estrogen if severe hypercalcemia, loss of vision, severe hypertriglyceridemia or cholestatic jaundice occurs (5.5, 5.6, 5.9, 5.10)
- Monitor thyroid function in women on thyroid replacement therapy (5.11, 5.18)

6 ADVERSE REACTIONS

Most common adverse reactions with norethindrone acetate and ethinyl estradiol tablets (incidence greater than or equal to 5 percent) are: headache, abdominal pain, breast pain, and edema (generalized). (6.1)

To report SUSPECTED ADVERSE REACTIONS, contact Glenmark Pharmaceuticals Inc., USA at 1 (888) 721-7115 or FDA at 1-800-FDA-1088 or www.fda.gov/medwatch.

7 DRUG INTERACTIONS

Inducers and/or inhibitors of CYP3A4 may affect estrogen drug metabolism and decrease or increase the estrogen plasma concentration. (7.1)

FULL PRESCRIBING INFORMATION

WARNING: CARDIOVASCULAR DISORDERS, PROBABLE DEMENTIA, BREAST CANCER, and ENDOMETRIAL CANCER

Estrogen Plus Progestin Therapy

Cardiovascular Disorders and Probable Dementia

The Women’s Health Initiative (WHI) estrogen plus progestin substudy reported increased risks of pulmonary embolism (PE), deep vein thrombosis (DVT), stroke, and myocardial infarction (MI) in postmenopausal women (50 to 79 years of age) during 5.6 years of treatment with daily oral conjugated estrogens (CE) [0.625 mg] combined with medroxyprogesterone acetate (MPA) [2.5 mg], relative to placebo [see Warnings and Precautions (5.1), and Clinical Studies (14.5)].

The WHI Memory Study (WHIMS) estrogen plus progestin ancillary study of WHI reported an increased risk of developing probable dementia in postmenopausal women 65 years of age and older during 4 years of treatment with daily CE (0.625 mg) combined with MPA (2.5 mg), relative to placebo. It is unknown whether this finding applies to younger postmenopausal women [see Warnings and Precautions (5.3), Use in Specific Populations (8.5), and Clinical Studies (14.6)].

Do not use estrogen plus progestogen therapy for the prevention of cardiovascular disease or dementia [see Warnings and Precautions (5.1, 5.3), and Clinical Studies (14.5, 14.6)].

Breast Cancer

The WHI estrogen plus progestin substudy demonstrated an increased risk of invasive breast cancer [see Warnings and Precautions (5.2) and Clinical Studies (14.5)].

Only daily oral 0.625 mg CE and 2.5 mg MPA were studied in the estrogen plus progestin substudy of the WHI. Therefore, the relevance of the WHI findings regarding adverse cardiovascular events, dementia and breast cancer to lower CE plus other MPA doses, other routes of administration, or other estrogen plus progestogen products is not known. Without such data, it is not possible to definitively exclude these risks or determine the extent of these risks for other products. Discuss with your patient the benefits and risks of estrogen plus progestogen therapy, taking into account her individual risk profile.

Prescribe estrogens with or without progestogens at the lowest effective doses and for the shortest duration consistent with treatment goals and risks for the individual woman.

Estrogen-Alone Therapy

Endometrial Cancer

There is an increased risk of endometrial cancer in a woman with a uterus who uses unopposed estrogens. Adding a progestogen to estrogen therapy has been shown to reduce the risk of endometrial hyperplasia, which may be a precursor to endometrial cancer. Perform adequate diagnostic measures, including directed or random endometrial sampling when indicated, to rule out malignancy in postmenopausal women with undiagnosed persistent or recurring abnormal genital bleeding [see Warnings and Precautions (5.2)].

Cardiovascular Disorders and Probable Dementia

The WHI estrogen-alone substudy reported increased risks of stroke and DVT in postmenopausal women (50 to 79 years of age) during 7.1 years of treatment with daily oral CE (0.625 mg)-alone, relative to placebo [see Warnings and Precautions (5.1) and Clinical Studies (14.5)].

The WHIMS estrogen-alone ancillary study of the WHI reported an increased risk of developing probable dementia in postmenopausal women 65 years of age and older during 5.2 years of treatment with daily CE (0.625 mg)-alone, relative to placebo. It is unknown whether this finding applies to younger postmenopausal women [see Warnings and Precautions (5.3), Use in Specific Populations (8.5) and Clinical Studies (14.6)].

Do not use estrogen-alone therapy for the prevention of cardiovascular disease or dementia [see Warnings and Precautions (5.1, 5.3), and Clinical Studies (14.5, 14.6)].

Only daily oral 0.625 mg CE was studied in the estrogen-alone substudy of the WHI. Therefore, the relevance of the WHI findings regarding adverse cardiovascular events and dementia to lower CE doses, other routes of administration, or other estrogen-alone products is not known. Without such data, it is not possible to definitively exclude these risks or determine the extent of these risks for other products. Discuss with your patient the benefits and risks of estrogen-alone therapy, taking into account her individual risk profile.

Prescribe estrogens with or without progestogens at the lowest effective doses and for the shortest duration consistent with treatment goals and risks for the individual woman.

1 INDICATIONS AND USAGE

1.2 Prevention of Postmenopausal Osteoporosis

Limitation of Use

When prescribing solely for the prevention of postmenopausal osteoporosis, first consider the use of non-estrogen medications. Consider estrogen therapy only for women at significant risk of osteoporosis.

2 DOSAGE AND ADMINISTRATION

Use estrogen, alone or in combination with a progestogen, at the lowest effective dose and for the shortest duration consistent with treatment goals and risks for the individual woman. Re-evaluate postmenopausal women periodically as clinically appropriate to determine whether treatment is still necessary.

2.1 Treatment of Moderate to Severe Vasomotor Symptoms due to Menopause

Take a single norethindrone acetate and ethinyl estradiol tablet, orally once daily.

2.2 Prevention of Postmenopausal Osteoporosis

Take a single norethindrone acetate and ethinyl estradiol tablet, orally once daily

3 DOSAGE FORMS AND STRENGTHS

The following two strengths of Norethindrone Acetate and Ethinyl Estradiol Tablets, USP are available:

Norethindrone Acetate and Ethinyl Estradiol Tablets, USP (0.5 mg/2.5 mcg): Each light pink to pink, round, flat-faced beveled edge, uncoated tablet contains 0.5 mg norethindrone acetate, USP and 2.5 mcg ethinyl estradiol, USP; debossed with ‘D5’ on one side and plain on the other side.

Norethindrone Acetate and Ethinyl Estradiol Tablets, USP (1 mg/5 mcg): Each white to off-white, round, flat-faced beveled edge, uncoated tablet contains 1 mg norethindrone acetate, USP and 5 mcg ethinyl estradiol, USP; debossed with ‘D6’ on one side and plain on the other side.

4 CONTRAINDICATIONS

Norethindrone acetate and ethinyl estradiol tablets are contraindicated in women with any of the following conditions:

- Undiagnosed abnormal genital bleeding [see Warnings and Precautions (5.2)].
- Breast cancer or a history of breast cancer [see Warnings and Precautions (5.2)].
- Estrogen-dependent neoplasia [see Warnings and Precautions (5.2)].
- Active DVT, PE or a history of these conditions [see Warnings and Precautions (5.1)].
- Active arterial thromboembolic disease (for example, stroke and MI), or a history of these conditions [see Warnings and Precautions (5.1)].
- Known anaphylactic reaction, angioedema, or hypersensitivity to norethindrone acetate and ethinyl estradiol tablets.
- Hepatic impairment or disease.
- Protein C, protein S, or antithrombin deficiency, or other known thrombophilic disorders.

5 WARNINGS AND PRECAUTIONS

5.1 Cardiovascular Disorders

Increased risk of PE, DVT, stroke, and MI are reported with estrogen plus progestin therapy. Increased risks of stroke and DVT are reported with estrogen-alone therapy. Immediately discontinue estrogen with or without progestogen therapy if any of these occur or are suspected.

Manage appropriately any risk factors for arterial vascular disease (for example, hypertension, diabetes mellitus, tobacco use, hypercholesterolemia, and obesity) and/or venous thromboembolism (VTE) (for example, personal history or family history of VTE, obesity, and systemic lupus erythematosus).

Stroke

The WHI estrogen plus progestin substudy reported a statistically significant increased risk of stroke in women 50 to 79 years of age receiving daily CE (0.625 mg) plus MPA (2.5 mg) compared to women in the same age group receiving placebo (33 versus 25 strokes per 10,000 women- years) [see Clinical Studies (14.5)]. The increase in risk was demonstrated after the first year and persisted.^1 Immediately discontinue estrogen with or without progestogen therapy if a stroke occurs or is suspected.

The WHI estrogen-alone substudy, reported a statistically significant increased risk of stroke in women 50 to 79 years of age receiving daily conjugated estrogens CE (0.625 mg)-alone compared to women in the same age group receiving placebo (45 versus 33 per 10,000 women-years). The increase in risk was demonstrated in year 1 and persisted [see Clinical Studies (14.5)]. Immediately discontinue estrogen-alone therapy if a stroke occurs or is suspected.

Subgroup analyses of women 50 to 59 years of age suggest no increased risk of stroke for those women receiving CE (0.625 mg)-alone versus those receiving placebo (18 versus 21 per 10,000 women-years).^1

Coronary Heart Disease

The WHI estrogen plus progestin substudy reported an increased risk (not statistically significant) of coronary heart disease (CHD) events (defined as nonfatal MI, silent MI, or CHD death) in those women receiving daily CE (0.625 mg) plus MPA (2.5 mg) compared to women receiving placebo (41 versus 34 per 10,000 women-years).^1 An increase in relative risk was demonstrated in year 1, and a trend toward decreasing relative risk was reported in years 2 through 5 [see Clinical Studies (14.5)].

The WHI estrogen-alone substudy reported no overall effect on CHD events in women receiving estrogen-alone compared to placebo^2 [see Clinical Studies (14.5)].

Subgroup analyses of women 50 to 59 years of age, who were less than 10 years since menopause, suggest a reduction (not statistically significant) of CHD events in those women receiving CE (0.625 mg)-alone compared to placebo (8 versus 16 per 10,000 woman-years).^1

In postmenopausal women with documented heart disease (n = 2,763), average 66.7 years of age, in a controlled clinical trial of secondary prevention of cardiovascular disease (Heart and Estrogen/Progestin Replacement Study [HERS]), treatment with daily CE (0.625 mg) plus MPA (2.5 mg) demonstrated no cardiovascular benefit. During an average follow-up of 4.1 years, treatment with CE plus MPA did not reduce the overall rate of CHD events in postmenopausal women with established CHD. There were more CHD events in the CE plus MPA-treated group than in the placebo group in year 1, but not during the subsequent years. Two thousand, three hundred and twenty-one (2,321) women from the original HERS trial agreed to participate in an open label extension of HERS, HERS II. Average follow-up in HERS II was an additional 2.7 years, for a total of 6.8 years overall. Rates of CHD events were comparable among women in the CE plus MPA group and the placebo group in HERS, HERS II, and overall.

Venous Thromboembolism

The WHI estrogen plus progestin substudy reported a statistically significant 2-fold greater rate of VTE (DVT and PE) in women receiving daily CE (0.625 mg) plus MPA (2.5 mg) compared to women receiving placebo (35 versus 17 per 10,000 women-years). Statistically significant increases in risk for both DVT (26 versus 13 per 10,000 women-years) and PE (18 versus 8 per 10,000 women-years) were also demonstrated. The increase in VTE risk was demonstrated during the first year and persisted^3 [see Clinical Studies (14.5)]. Immediately discontinue estrogen plus progestogen therapy if a VTE occurs or is suspected.

In the WHI estrogen-alone substudy, the risk of VTE was increased for women receiving daily CE (0.625 mg)-alone compared to placebo (30 versus 22 per 10,000 women-years), although only the increased risk of DVT reached statistical significance (23 versus 15 per 10,000 women-years). The increase in VTE risk was demonstrated during the first 2 years^4 [see Clinical Studies (14.5)]. Immediately discontinue estrogen-alone therapy if a VTE occurs or is suspected.

If feasible, discontinue estrogens at least 4 to 6 weeks before surgery of the type associated with an increased risk of thromboembolism or during periods of prolonged immobilization.

5.2 Malignant Neoplasms

Breast Cancer

After a mean follow-up of 5.6 years, the WHI substudy of daily CE (0.625 mg) plus MPA (2.5 mg) reported an increased risk of invasive breast cancer in women who took daily CE plus MPA compared to placebo. In this substudy, prior use of estrogen-alone or estrogen plus progestin therapy was reported by 26 percent of the women. The relative risk of invasive breast cancer was 1.24, and the absolute risk was 41 versus 33 cases per 10,000 women-years for CE plus MPA compared with placebo [see Clinical Studies (14.5)]. Among women who reported prior use of hormone therapy, the relative risk of invasive breast cancer was 1.86 and the absolute risk was 46 versus 25 cases per 10,000 women-years for CE plus MPA compared with placebo. Among women who reported no prior use of hormone therapy, the relative risk of invasive breast cancer was 1.09, and the absolute risk was 40 versus 36 cases per 10,000 women-years for CE plus MPA compared with placebo. In the same substudy, invasive breast cancers were larger, were more likely to be node positive, and were diagnosed at a more advanced stage in the CE (0.625 mg) plus MPA (2.5 mg) group compared with the placebo group. Metastatic disease was rare with no apparent difference between the two groups. Other prognostic factors, such as histologic subtype, grade and hormone receptor status did not differ between the groups^5 [see Clinical Studies (14.5)].

The WHI substudy of daily CE (0.625 mg)-alone provided information about breast cancer in estrogen-alone users. In the WHI estrogen-alone substudy, after an average follow up of 7.1 years, daily CE-alone was not associated with an increased risk of invasive breast cancer (relative risk [RR] 0.80 compared to placebo^6 [see Clinical Studies (14.5)].

Consistent with the WHI clinical trials, observational studies have also reported an increased risk of breast cancer for estrogen plus progestin therapy, and a smaller increased risk for estrogen-alone therapy, after several years of use. One large meta-analysis of prospective cohort studies reported increased risks that were dependent upon duration of use and could last up to >10 years after discontinuation of estrogen plus progestin therapy and estrogen-alone therapy. Extension of the WHI trials also demonstrated increased breast cancer risk associated with estrogen plus progestin therapy. Observational studies also suggest that the risk of breast cancer was greater, and became apparent earlier, with estrogen plus progestin therapy as compared to estrogen-alone therapy. These studies have not generally found significant variation in the risk of breast cancer among different estrogen plus progestin combinations, doses, or routes of administration.

The use of estrogen-alone and estrogen plus progestin has been reported to result in an increase in abnormal mammograms requiring further evaluation.

All women should receive yearly breast examinations by a healthcare provider and perform monthly breast self-examinations. In addition, mammography examinations should be scheduled based on patient age, risk factors and prior mammogram results.

Endometrial Cancer

Endometrial hyperplasia (a possible precursor of endometrial cancer) has been reported to occur at a rate of approximately 1 percent or less with norethindrone acetate and ethinyl estradiol tablets.

An increased risk of endometrial cancer has been reported with the use of unopposed estrogen therapy in a woman with a uterus. The reported endometrial cancer risk among unopposed estrogen users is about 2 to 12 times greater than in non-users, and appears dependent on duration of treatment and on estrogen dose. Most studies show no significant increased risk associated with use of estrogens for less than 1 year. The greatest risk appears associated with prolonged use, with increased risks of 15- to 24-fold for 5 to 10 years or more. This risk has been shown to persist for at least 8 to 15 years after estrogen therapy is discontinued.

Clinical surveillance of all women using estrogen-alone or estrogen plus progestogen therapy is important. Adequate diagnostic measures, including directed or random endometrial sampling when indicated, should be undertaken to rule out malignancy in postmenopausal women with undiagnosed persistent or recurring abnormal genital bleeding.

There is no evidence that the use of natural estrogens results in a different endometrial risk profile than synthetic estrogens of equivalent estrogen dose. Adding a progestogen to estrogen therapy in postmenopausal women has been shown to reduce the risk of endometrial hyperplasia, which may be a precursor to endometrial cancer.

Ovarian Cancer

The CE plus MPA substudy of WHI reported that estrogen plus progestin increased the risk of ovarian cancer. After an average follow-up of 5.6 years, the relative risk for ovarian cancer for CE plus MPA versus placebo was 1.58 (95 percent CI, 0.77 to 3.24), but it was not statistically significant. The absolute risk for CE plus MPA versus placebo was 4 versus 3 cases per 10,000 women-years.^7

A meta-analysis of 17 prospective and 35 retrospective epidemiology studies found that women who used hormonal therapy for menopausal symptoms had an increased risk for ovarian cancer. The primary analysis, using case-control comparisons, included 12,110 cancer cases from the 17 prospective studies. The relative risks associated with current use of hormonal therapy was 1.41 (95% confidence interval [CI] 1.32 to 1.50); there was no difference in the risk estimates by duration of the exposure (less than 5 years [median of 3 years] vs. greater than 5 years [median of 10 years] of use before the cancer diagnosis). The relative risk associated with combined current and recent use (discontinued use within 5 years before cancer diagnosis) was 1.37 (95% CI 1.27 to 1.48), and the elevated risk was significant for both estrogen-alone and estrogen plus progestin products. The exact duration of hormone therapy use associated with an increased risk of ovarian cancer, however, is unknown.

5.3 Probable Dementia

In the WHI Memory Study (WHIMS) estrogen plus progestin ancillary study, a population of 4,532 postmenopausal women 65 to 79 years of age was randomized to daily CE (0.625 mg) plus MPA (2.5 mg) or placebo.

After an average follow-up of 4 years, 40 women in the CE plus MPA group and 21 women in the placebo group were diagnosed with probable dementia. The relative risk of probable dementia for CE plus MPA versus placebo was 2.05 (95 percent CI, 1.21 to 3.48). The absolute risk of probable dementia for CE plus MPA versus placebo was 45 versus 22 cases per 10,000 women-years^8 [see Use in Specific Populations (8.5), and Clinical Studies (14.6)].

In the WHIMS estrogen-alone ancillary study, a population of 2,947 hysterectomized women 65 to 79 years of age was randomized to daily CE (0.625 mg)-alone or placebo.

After an average follow-up of 5.2 years, 28 women in the estrogen-alone group and 19 women in the placebo group were diagnosed with probable dementia. The relative risk of probable dementia for CE-alone versus placebo was 1.49 (95 percent CI, 0.83 to 2.66). The absolute risk of probable dementia for CE-alone versus placebo was 37 versus 25 cases per 10,000 women-years^8 [see Use in Specific Populations (8.5), and Clinical Studies (14.6)].

When data from the two populations in the WHIMS estrogen-alone and estrogen plus progestin ancillary studies were pooled as planned in the WHIMS protocol, the reported overall relative risk for probable dementia was 1.76 (95 percent CI, 1.19 to 2.6). Since both ancillary substudies were conducted in women 65 to 79 years of age, it is unknown whether these findings apply to younger postmenopausal women^8 [see Use in Specific Populations (8.5), and Clinical Studies (14.6)].

5.4 Gallbladder Disease

A 2- to 4-fold increase in the risk of gallbladder disease requiring surgery in postmenopausal women receiving estrogens has been reported.

5.5 Hypercalcemia

Estrogen administration may lead to severe hypercalcemia in women with breast cancer and bone metastases. Discontinue estrogens, including norethindrone acetate and ethinyl estradiol tablets, if hypercalcemia occurs, and take appropriate measures to reduce the serum calcium level.

5.6 Visual Abnormalities

Retinal vascular thrombosis has been reported in women receiving estrogens. Discontinue norethindrone acetate and ethinyl estradiol tablets pending examination if there is sudden partial or complete loss of vision, or a sudden onset of proptosis, diplopia, or migraine. Permanently discontinue estrogens, including norethindrone acetate and ethinyl estradiol tablets, if examination reveals papilledema or retinal vascular lesions.

5.7 Addition of a Progestogen When a Woman Has Not Had a Hysterectomy

Studies of the addition of a progestogen for 10 or more days of a cycle of estrogen administration or daily with estrogen in a continuous regimen, have reported a lowered incidence of endometrial hyperplasia than would be induced by estrogen treatment alone. Endometrial hyperplasia may be a precursor to endometrial cancer.

There are, however, possible risks that may be associated with the use of progestogens with estrogens compared to estrogen-alone regimens. These include an increased risk of breast cancer.

5.8 Elevated Blood Pressure

In a small number of case reports, substantial increases in blood pressure have been attributed to idiosyncratic reactions to estrogens. In a large, randomized, placebo-controlled clinical trial, a generalized effect of estrogen therapy on blood pressure was not seen.

5.9 Exacerbation of Hypertriglyceridemia

In women with pre-existing hypertriglyceridemia, estrogen therapy may be associated with elevations of plasma triglycerides leading to pancreatitis. Discontinue norethindrone acetate and ethinyl estradiol tablets if pancreatitis occurs.

5.10 Hepatic Impairment and/or a Past History of Cholestatic Jaundice

Estrogens may be poorly metabolized in women with hepatic impairment. Exercise caution in any women with a history of cholestatic jaundice associated with past estrogen use or with pregnancy. In the case of recurrence of cholestatic jaundice, discontinue norethindrone acetate and ethinyl estradiol tablets.

5.11 Exacerbation of Hypothyroidism

Estrogen administration leads to increased thyroid-binding globulin (TBG) levels. Women with normal thyroid function can compensate for the increased TBG by making more thyroid hormone, thus maintaining free T4 and T3 serum concentrations in the normal range. Women dependent on thyroid hormone replacement therapy who are also receiving estrogen may require increased doses of their thyroid replacement therapy. Monitor thyroid function in these women during treatment with norethindrone acetate and ethinyl estradiol tablets to maintain their free thyroid hormone levels in an acceptable range.

5.12 Fluid Retention

Estrogens plus progestogens may cause some degree of fluid retention. Monitor any women with condition(s) that might predispose her to fluid retention, such as cardiac or renal impairment. Discontinue estrogen plus progestogen therapy, including norethindrone acetate and ethinyl estradiol tablets, with evidence of medically concerning fluid retention.

5.13 Hypocalcemia

Estrogen-induced hypocalcemia may occur in women with hypoparathyroidism. Consider whether the benefits of estrogen therapy, including norethindrone acetate and ethinyl estradiol tablets, outweigh the risks in such women.

5.14 Exacerbation of Endometriosis

A few cases of malignant transformation of residual endometrial implants have been reported in women treated post-hysterectomy with estrogen-alone therapy.

5.15 Hereditary Angioedema

Exogenous estrogens may exacerbate symptoms of angioedema in women with hereditary angioedema. Consider whether the benefits of estrogen therapy, including norethindrone acetate and ethinyl estradiol tablets, outweigh the risks in such women.

5.16 Exacerbation of Other Conditions

Estrogen therapy, including norethindrone acetate and ethinyl estradiol tablets, may cause an exacerbation of asthma, diabetes mellitus, epilepsy, migraine, porphyria, systemic lupus erythematosus and hepatic hemangiomas. Consider whether the benefits of estrogen therapy outweigh the risks in women with such conditions.

5.17 Laboratory Tests

Serum follicle stimulating hormone (FSH) and estradiol levels have not been shown to be useful in the management of postmenopausal women with moderate to severe vasomotor symptoms.

5.18 Drug-Laboratory Test Interactions

Accelerated prothrombin time, partial thromboplastin time, and platelet aggregation time; increased platelet count; increased factors II, VII antigen, VIII antigen, VIII coagulant activity, IX, X, XII, VII-X complex, II-VII-X complex, and beta-thromboglobulin; decreased levels of antifactor Xa and antithrombin III, decreased antithrombin III activity; increased levels of fibrinogen and fibrinogen activity; increased plasminogen antigen and activity.

Increased TBG levels leading to increased circulating total thyroid hormone levels as measured by protein-bound iodine (PBI), T4 levels (by column or by radioimmunoassay) or T3 levels by radioimmunoassay. T3 resin uptake is decreased, reflecting the elevated TBG. Free T4 and free T3 concentrations are unaltered. Women on thyroid replacement therapy may require higher doses of thyroid hormone.

Other binding proteins may be elevated in serum, for example, corticosteroid binding globulin (CBG), sex hormone-binding globulin (SHBG), leading to increased total circulating corticosteroids and sex steroids, respectively. Norethindrone acetate and ethinyl estradiol tablets 1/5 was associated with an SHBG increase of 22 percent. Free hormone concentrations, such as testosterone and estradiol, may be decreased. Other plasma proteins may be increased (angiotensinogen/renin substrate, alpha-1-antitrypsin, ceruloplasmin).

Increased plasma high-density lipoprotein (HDL) and HDL2 cholesterol subfraction concentrations, reduced low-density lipoprotein (LDL) cholesterol concentration, increased triglycerides levels.

Impaired glucose tolerance.

6 ADVERSE REACTIONS

The following serious adverse reactions are discussed elsewhere in the labeling:

- Cardiovascular Disorders [see Boxed Warning, Warnings and Precautions (5.1)].
- Malignant Neoplasms [see Boxed Warning, Warnings and Precautions (5.2)].

6.1 Clinical Trials Experience

Because clinical trials are conducted under widely varying conditions, adverse reaction rates observed in the clinical trials of a drug cannot be directly compared to rates in the clinical trials of another drug and may not reflect the rates observed in practice.

Adverse reactions reported by ≥5 percent of women in controlled clinical studies of norethindrone acetate and ethinyl estradiol tablets are shown in Table 1.

Table 1. Associated Adverse Reactions Reported by ≥5 Percent of Women by Body System*

BODY SYSTEM/ Adverse Reaction | Number (Percent) of Subjects
BODY SYSTEM/ Adverse Reaction | Placebo | Norethindrone Acetate and Ethinyl Estradiol Tablets 0.5/2.5 | Norethindrone Acetate and Ethinyl Estradiol Tablets 1/5
BODY SYSTEM/ Adverse Reaction | N = 247 | N = 244 | N = 258
BODY AS A WHOLE | 23 (12.8) | 30 (16.9) | 30 (15.7)
Edema - Generalized | 10 (4) | 12 (4.9) | 11 (4.3)
Headache | 12 (4.9) | 14 (5.7) | 16 (6.2)
DIGESTIVE SYSTEM | 8 (4.4) | 17 (9.6) | 25 (13.1)
Abdominal Pain | 3 (1.2) | 13 (5.3) | 14 (6.8)
UROGENITAL SYSTEM | 20 (11.1) | 34 (19.2) | 45 (23.6)
Breast Pain | 9 (3.6) | 22 (9) | 20 (7.8)

*The total number of women for each body system may be less than the number of women with AEs in that body system because a women may have had more than one AE per body system

6.2 Postmarketing Experience

The following additional adverse reactions have been identified during post-approval use of norethindrone acetate and ethinyl estradiol tablets. Because these reactions are reported voluntarily from a population of uncertain size, it is not always possible to reliably estimate their frequency or establish a causal relationship to drug exposure.

Genitourinary System

Changes in vaginal bleeding pattern and abnormal withdrawal bleeding or flow; breakthrough bleeding; spotting; increase in size of uterine leiomyomata, vaginitis, including vaginal candidiasis; change in amount of cervical secretion; changes in cervical ectropion; ovarian cancer; endometrial hyperplasia; endometrial cancer; uterine cancer; vaginal hemorrhage; ovarian cyst; irregular menstruation; metrorrhagia; menorrhagia; dysmenorrhea; uterine enlargement.

Breasts

Tenderness, enlargement, breast pain, nipple pain, nipple discharge, galactorrhea; fibrocystic breast changes; breast cancer; breast disorder; breast mass; breast enlargement.

Cardiovascular

Deep and superficial venous thrombosis; pulmonary embolism; thrombophlebitis; thrombosis; chest pain; myocardial infarction; cerebrovascular accident (stroke); transient ischemic attack; hemiparesis; increase in blood pressure; irregular heart rate; palpitations; dyspnea.

Gastrointestinal

Nausea, vomiting; cholestatic jaundice; pancreatitis, enlargement of hepatic hemangiomas; bloating, abdominal cramps; abdominal pain; increased incidence of gallbladder disease; cholecystitis; cholelithiasis.

Skin

Chloasma or melasma that may persist when drug is discontinued; generalized erythema; erythema multiforme; erythema nodosum; hemorrhagic eruption; loss of scalp hair; hirsutism; rash, pruritus.

Eyes

Retinal vascular thrombosis; visual impairment; intolerance to contact lenses.

Central Nervous System (CNS)

Headache; migraine; dizziness; depression; chorea; nervousness; mood disturbances; irritability; exacerbation of epilepsy, dementia; paresthesia; insomnia.

Miscellaneous

Increase or decrease in weight; reduced carbohydrate tolerance; aggravation of porphyria; edema; arthralgias; leg cramps; back pain; changes in libido; urticaria, angioedema, anaphylactoid/anaphylactic reactions; hypocalcemia; exacerbation of asthma; increased triglycerides; blood glucose abnormal; fatigue; myalgia; hypersensitivity.

7 DRUG INTERACTIONS

In vitro and in vivo studies have shown that estrogens are metabolized partially by cytochrome P450 3A4 (CYP3A4). Therefore, inducers or inhibitors of CYP3A4 may affect estrogen and progestin drug metabolism. Inducers of CYP3A4 such as St. John’s wort (Hypericum perforatum) preparations, phenobarbital, carbamazepine and rifampin may decrease the plasma concentration of estrogens and progestins, possibly resulting in a decrease in therapeutic effects and/or changes in the uterine bleeding profile. Inhibitors of CYP3A4 such as erythromycin, clarithromycin, ketoconazole, itraconazole, ritonavir and grapefruit juice may increase the plasma concentration of the estrogen or the progestin or both and may result in adverse reactions.

Co-administration of atorvastatin and certain hormonal products containing ethinyl estradiol increase AUC values for ethinyl estradiol approximately 20 percent. Ascorbic acid and acetaminophen may increase the plasma ethinyl estradiol concentration, possibly by inhibition of conjugation.

Combination hormonal products have been shown to significantly decrease the plasma concentration of lamotrigine likely due to induction of lamotrigine glucuronidation. This may reduce seizure control; therefore, dosage adjustments of lamotrigine may be necessary.

8 USE IN SPECIFIC POPULATIONS

8.1 Pregnancy

Risk Summary

Norethindrone acetate and ethinyl estradiol tablets are not indicated for use in pregnancy. There are no data with the use of norethindrone acetate and ethinyl estradiol tablets in pregnant women; however, epidemiologic studies and meta-analyses have not found an increased risk of genital or nongenital birth defects (including cardiac anomalies and limb-reduction defects) following exposure to combined (estrogens and progestins) product before conception or during early pregnancy.

In the U.S. general population, the estimated background risk of major birth defects and miscarriage in clinically recognized pregnancies is 2% to 4% and 15% to 20%, respectively.

8.2 Lactation

Risk Summary

Estrogens plus progestogens are present in human milk and can reduce milk production in breast-feeding women. This reduction can occur at any time but is less likely to occur once breast-feeding is well-established. The development and health benefits of breastfeeding should be considered along with the mother’s clinical need for norethindrone acetate and ethinyl estradiol tablets and any potential adverse effects on the breastfed child from norethindrone acetate and ethinyl estradiol tablets or from the underlying maternal condition.

8.4 Pediatric Use

Norethindrone acetate and ethinyl estradiol tablets are not indicated for use in pediatric patients. Clinical studies have not been conducted in the pediatric population.

8.5 Geriatric Use

There have not been sufficient numbers of geriatric women involved in clinical studies utilizing norethindrone acetate and ethinyl estradiol tablets to determine whether those over 65 years of age differ from younger subjects in their response to norethindrone acetate and ethinyl estradiol tablets.

The Women’s Health Initiative Studies

In the WHI estrogen plus progestin substudy (daily CE [0.625 mg] plus MPA [2.5 mg] versus placebo), there was a higher relative risk of nonfatal stroke and invasive breast cancer in women greater than 65 years of age [see Clinical Studies (14.5)].

In the WHI estrogen-alone substudy (daily CE [0.625 mg]-alone versus placebo), there was a higher relative risk of stroke in women greater than 65 years of age [see Clinical Studies (14.5)].

The Women’s Health Initiative Memory Study

In the WHIMS ancillary studies of postmenopausal women 65 to 79 years of age, there was an increased risk of developing probable dementia in women receiving estrogen plus progestin or estrogen-alone when compared to placebo [see Warnings and Precautions (5.3), and Clinical Studies (14.6)].

Since both ancillary studies were conducted in women 65 to 79 years of age, it is unknown whether these findings apply to younger postmenopausal women8 [see Warnings and Precautions (5.3), and Clinical Studies (14.6)].

10 OVERDOSAGE

Overdosage of estrogen plus progestogen may cause nausea, vomiting, breast tenderness, abdominal pain, drowsiness and fatigue, and withdrawal bleeding may occur in women. Treatment of overdose consists of discontinuation of norethindrone acetate and ethinyl estradiol tablets therapy with institution of appropriate symptomatic care.

11 DESCRIPTION

Norethindrone Acetate and Ethinyl Estradiol Tablets, USP is a continuous dosage regimen of a progestin-estrogen combination for oral administration.

The following two strengths of Norethindrone Acetate and Ethinyl Estradiol Tablets, USP are available as:

Norethindrone Acetate and Ethinyl Estradiol Tablets USP (0.5 mg/2.5 mcg): Each light pink to pink, round, flat-faced beveled edge, uncoated tablet contains 0.5 mg norethindrone acetate, USP and 2.5 mcg ethinyl estradiol, USP.

Norethindrone Acetate and Ethinyl Estradiol Tablets USP (1 mg/5 mcg): Each white to off-white, round, flat-faced beveled edge, uncoated tablet contains 1 mg norethindrone acetate, USP and 5 mcg ethinyl estradiol, USP.

Each tablet also contains the following inactive ingredients: calcium stearate, cornstarch, lactose monohydrate, microcrystalline cellulose, povidone and vitamin E and talc. The 0.5 mg/2.5 mcg light pink to pink tablet also contains D&C red no. 30.

The structural formulas are as follows

Ethinyl Estradiol, USP [19-Nor-17α-pregna-1,3,5(10)-trien-20-yne-3,17-diol]

Molecular Weight: 296.40

Molecular Formula: C20H24O2

Norethindrone Acetate USP [19-Norpregn-4-en-20-yn-3-one, 17-(acetyloxy)-, (17 α)]

Molecular Weight: 340.46

Molecular Formula: C22H28O3

12 CLINICAL PHARMACOLOGY

12.1 Mechanism of Action

Endogenous estrogens are largely responsible for the development and maintenance of the female reproductive system and secondary sexual characteristics. Although circulating estrogens exist in a dynamic equilibrium of metabolic interconversions, estradiol is the principal intracellular human estrogen and is substantially more potent than its metabolites, estrone and estriol, at the receptor level.

The primary source of estrogen in normally cycling adult women is the ovarian follicle, which secretes 70 to 500 mcg of estradiol daily, depending on the phase of the menstrual cycle. After menopause, most endogenous estrogen is produced by conversion of androstenedione, which is secreted by the adrenal cortex, to estrone in the peripheral tissues. Thus, estrone and the sulfate conjugated form, estrone sulfate, are the most abundant circulating estrogens in postmenopausal women. The pharmacologic effects of ethinyl estradiol are similar to those of endogenous estrogens.

Estrogens act through binding to nuclear receptors in estrogen-responsive tissues. To date, two estrogen receptors have been identified. These vary in proportion from tissue to tissue.

Circulating estrogens modulate the pituitary secretion of the gonadotropins, luteinizing hormone (LH) and FSH through a negative feedback mechanism. Estrogens act to reduce the elevated levels of these hormones seen in postmenopausal women.

Progestin compounds enhance cellular differentiation and generally oppose the actions of estrogens by decreasing estrogen receptor levels, increasing local metabolism of estrogens to less active metabolites, or inducing gene products that blunt cellular responses to estrogen. Progestins exert their effects in target cells by binding to specific progesterone receptors that interact with progesterone response elements in target genes. Progesterone receptors have been identified in the female reproductive tract, breast, pituitary, hypothalamus, bone, skeletal tissue and central nervous system. Progestins produce similar endometrial changes to those of the naturally occurring hormone progesterone.

12.2 Pharmacodynamics

Generally, a serum estrogen concentration does not predict an individual woman’s therapeutic response to norethindrone acetate and ethinyl estradiol tablets nor her risk for adverse outcomes. Likewise, exposure comparisons across different estrogen products to infer efficacy or safety for the individual woman may not be valid.

12.3 Pharmacokinetics

Absorption

Norethindrone acetate (NA) is completely deacetylated to norethindrone after oral administration, and the disposition of norethindrone acetate is indistinguishable from that of orally administered norethindrone. Norethindrone acetate and ethinyl estradiol (EE) are absorbed from norethindrone acetate and ethinyl estradiol tablets, with maximum plasma concentrations of norethindrone and ethinyl estradiol generally occurring 1 to 2 hours postdose. Both are subject to first-pass metabolism after oral dosing, resulting in an absolute bioavailability of approximately 64 percent for norethindrone and 55 percent for ethinyl estradiol. Bioavailability of norethindrone acetate and ethinyl estradiol tablets is similar to that from solution for norethindrone and slightly less for ethinyl estradiol. Administration of norethindrone acetate and ethinyl estradiol tablets with a high fat meal decreases rate but not extent of ethinyl estradiol absorption. The extent of norethindrone absorption is increased by 27 percent following administration of norethindrone acetate and ethinyl estradiol tablets with food.

The full pharmacokinetic profile of norethindrone acetate and ethinyl estradiol tablets was not characterized due to assay sensitivity limitations. However, the multiple-dose pharmacokinetics were studied at a dose of 1 mg NA/10 mcg EE in 18 post-menopausal women. Mean plasma concentrations are shown below (Figure 1) and pharmacokinetic parameters are found in Table 2. Based on a population pharmacokinetic analysis, mean steady-state concentrations of norethindrone for 1 mg NA/5 mcg EE and 1/10 are slightly more than proportional to dose when compared to 0.5 mg NA/2.5 mcg EE tablets. It can be explained by higher SHBG concentrations. Mean steady-state plasma concentrations of ethinyl estradiol for the norethindrone acetate and ethinyl estradiol 0.5 /2.5 tablets and norethindrone acetate and ethinyl estradiol 1 /5 tablets are proportional to dose, but there is a less than proportional increase in steady-state concentrations for the NA/EE 1 /10 tablet.

Figure 1. Mean Steady-State (Day 87) Plasma Norethindrone and Ethinyl Estradiol Concentrations Following Continuous Oral Administration of 1 mg NA/10 mcg EE Tablets

Table 2. Mean (SD) Single-Dose (Day 1) and Steady-State (Day 87) Pharmacokinetic Parameters† Following Administration of 1 mg NA/10 mcg EE Tablets
 | Cmax | tmax | AUC (0 to 24) | CL/F | t1/2
NORETHINDRONE | ng/mL | hr | ng•hr/mL | mL/min | hr
Day 1 | 6 (3.3) | 1.8 (0.8) | 29.7 (16.5) | 588 (416) | 10.3 (3.7)
Day 87 | 10.7 (3.6) | 1.8 (0.8) | 81.8 (36.7) | 226 (139) | 13.3 (4.5)
ETHINYL ESTRADIOL | pg/mL | hr | pg•hr/mL | mL/min | hr
Day 1 | 33.5 (13.7) | 2.2 (1) | 339 (113) | ND‡ | ND‡
Day 87 | 38.3 (11.9) | 1.8 (0.7) | 471 (132) | 383 (119) | 23.9 (7.1)

†Cmax = Maximum plasma concentration; tmax = time of Cmax; AUC (0 to 24) = Area under the plasma concentration-time curve over the dosing interval; and CL/F = Apparent oral clearance;

t½ = Elimination half-life

‡ND = Not determined

Based on a population pharmacokinetic analysis, average steady-state concentrations (Css) of norethindrone and ethinyl estradiol for norethindrone acetate and ethinyl estradiol 1/5 tablets are estimated to be 2.6 ng/mL and 11.4 pg/mL, respectively. Css values of norethindrone and ethinyl estradiol for norethindrone acetate and ethinyl estradiol 0.5/2.5 tablets are estimated to be 1.1 ng/mL and 5.4 ng/mL, respectively.

The pharmacokinetics of ethinyl estradiol and norethindrone acetate were not affected by age, (age range 40 to 62 years), in the postmenopausal population studied.

Distribution

The distribution of exogenous estrogens is similar to that of endogenous estrogens. Estrogens are widely distributed in the body and are generally found in higher concentrations in the sex hormone target organs. Estrogens circulate in the blood largely bound to SHBG and albumin.

Volume of distribution of norethindrone and ethinyl estradiol ranges from 2 to 4 L/kg. Plasma protein binding of both steroids is extensive (greater than 95 percent); norethindrone binds to both albumin and SHBG, whereas ethinyl estradiol binds only to albumin. Although ethinyl estradiol does not bind to SHBG, it induces SHBG synthesis.

Metabolism

Exogenous estrogens are metabolized in the same manner as endogenous estrogens. Circulating estrogens exist in a dynamic equilibrium of metabolic interconversions. These transformations take place mainly in the liver. Estradiol is converted reversibly to estrone, and both can be converted to estriol, which is a major urinary metabolite. Estrogens also undergo enterohepatic recirculation via sulfate and glucuronide conjugation in the liver, biliary secretion of conjugates into the intestine, and hydrolysis in the intestine followed by reabsorption. In postmenopausal women, a significant proportion of the circulating estrogens exist as sulfate conjugates, especially estrone sulfate, which serves as a circulating reservoir for the formation of more active estrogens.

Norethindrone undergoes extensive biotransformation, primarily via reduction, followed by sulfate and glucuronide conjugation. The majority of metabolites in the circulation are sulfates, with glucuronides accounting for most of the urinary metabolites. A small amount of norethindrone acetate is metabolically converted to ethinyl estradiol, such that exposure to ethinyl estradiol following administration of 1 mg of norethindrone acetate is equivalent to oral administration of 2.8 mcg ethinyl estradiol. Ethinyl estradiol is also extensively metabolized, both by oxidation and by conjugation with sulfate and glucuronide. Sulfates are the major circulating conjugates of ethinyl estradiol and glucuronides predominate in urine. The primary oxidative metabolite is 2-hydroxy ethinyl estradiol, formed by the CYP3A4 isoform of cytochrome P450. Part of the first-pass metabolism of ethinyl estradiol is believed to occur in gastrointestinal mucosa. Ethinyl estradiol may undergo enterohepatic circulation.

Excretion

Estradiol, estrone, and estriol are excreted in the urine along with glucuronide and sulfate conjugates.

Norethindrone and ethinyl estradiol are excreted in both urine and feces, primarily as metabolites. Plasma clearance values for norethindrone and ethinyl estradiol are similar (approximately 0.4 L/hr/kg). Steady-state elimination half-lives of norethindrone and ethinyl estradiol following administration of 1 mg NA/10 mcg EE tablets are approximately 13 hours and 24 hours, respectively.

13 NONCLINICAL TOXICOLOGY

13.1 Carcinogenesis, Mutagenesis, Impairment of Fertility

Long-term continuous administration of natural and synthetic estrogens in certain animal species increases the frequency of carcinomas of the breast, uterus, cervix, vagina, testis, and liver.

14 CLINICAL STUDIES

14.1 Effects on Vasomotor Symptoms in Postmenopausal Women

A 12-week placebo-controlled, multicenter, randomized clinical trial was conducted in 266 symptomatic women who had at least 56 moderate to severe hot flushes during the week prior to randomization. On average, women had 12 hot flushes per day upon study entry.

A total of 66 women were randomized to receive norethindrone acetate and ethinyl estradiol tablets 1/5 and 66 women were randomized to the placebo group. Norethindrone acetate and ethinyl estradiol tablets 1/5 was shown to be statistically better than placebo at weeks 4, and 12 for relief of the frequency of moderate to severe vasomotor symptoms (see Table 3). In Table 4, norethindrone acetate and ethinyl estradiol tablets 1 /5 was shown to be statistically better than placebo at weeks 4 and 12 for relief of the severity of moderate to severe vasomotor symptoms.

Table 3. Mean Change from Baseline in the Number of Moderate to Severe Vasomotor Symptoms per Week -ITT Population, LOCF

Visit | Placebo (N = 66) | Norethindrone Acetate and Ethinyl Estradiol Tablets; 0.5 /2.5 (N = 67) | Norethindrone Acetate and Ethinyl Estradiol Tablets 1 /5 (N = 66)
Baseline [1]
Mean (SD) | 76.5 (21.4) | 77.6 (26.5) | 70 (16.6)
Week 4
Mean (SD) | 39.4 (27.6) | 30.2 (26.1) | 20.4 (22.7)
Mean Change From Baseline (SD) | -37 (26.6) | -47.4è (26.1) | -49.6è (22.1)
p-Value vs. Placebo (95 percent CI) [2] |  | 0.041 (-20, -1) | <0.001 (-22, -6)
Week 12
Mean (SD) | 31.1 (27) | 13.8 (20.4) | 11.3 (18.9)
Mean Change from Baseline (SD) | -45.3 (30.2) | -63.8è (27.5) | -58.7è (23.1)
p-Value vs. Placebo (95 percent CI) [2] |  | <0.001 (-27, -7) | <0.001 (-25, -5)

è Denotes statistical significance at the 0.05 level

[1] The baseline number of moderate to severe vasomotor symptoms (MSVS) is the weekly average number of MSVS during the two week pre-randomization observation period.

[2] ANCOVA -Analysis of Covariance model where the observation variable is change from baseline; independent variables include treatment, center and baseline as covariate. The 95 percent CI -Mann-Whitney confidence interval for the difference between means (not stratified by center). ITT = intent to treat; LOCF last observation carried forward; CI = confidence interval 2 randomized subjects (1 in Placebo and 1 in norethindrone acetate and ethinyl estradiol tablets) did not return diaries.

Table 4. Mean Change from Baseline in the Daily Severity Score of Moderate to Severe
Vasomotor Symptoms per Week - ITT Population, LOCF

Visit | Placebo (N = 66) | Norethindrone Acetate and Ethinyl Estradiol Tablets 0.5 /2.5; (N = 67) | Norethindrone Acetate and Ethinyl Estradiol Tablets 1 /5 (N = 66)
Baseline [1]
Mean (SD) | 2.49 (0.26) | 2.48 (0.22) | 2.47 (0.23)
Week 4
Mean (SD) | 2.13 (0.74) | 1.88 (0.89) | 1.45 (1.03)
Mean Change from Baseline (SD) | -0.36 (0.68) | -0.59 (0.83) | -1.02¥ (1.06)
p-Value vs Placebo (95 percent CI) [2] | - | 0.130 (-0.3, 0) | <0.001 (-0.9, -0.2)
Week 5
Mean (SD) | 2.06 (0.79) | 1.68 (0.99) | 1.23 (1.03)
Mean Change from Baseline (SD) | -0.44 (0.74) | -0.8¥ (0.94) | -1.24¥ (1.07)
p-Value vs Placebo (95 percent CI) [2] | - | 0.041 (-0.4, -0) | <0.001 (-1.2, -0.3)
Week 12
Mean (SD) | 1.82 (1.03) | 1.22 (1.11) | 1.02 (1.16)
Mean Change from Baseline (SD) | -0.67 (1.02) | -1.26¥ (1.08) | -1.45¥ (1.19)
p-Value vs Placebo (95 percent CI) [2] | - | 0.002 (-0.9, -0.2) | <0.001 (-1.4, -0.3)

¥ Denotes statistical significance at the 0.05 level

[1] The baseline severity of moderate to severe vasomotor symptoms (MSVS) is the daily severity score of MSVS during the two week pre-randomization observation period.

[2] ANCOVA - Analysis of Covariance model where the observation variable is change from baseline; independent variables include treatment, center and baseline as covariate. The 95 percent CI - Mann-Whitney confidence interval for the difference between means (not stratified by center).

ITT = intent to treat; LOCF = last observation carried forward; CI = confidence interval 2 randomized women (1 in Placebo and 1 in norethindrone acetate and ethinyl estradiol tablets) did not return diaries.

14.2 Effects on the Endometrium

A 2-year, placebo-controlled, multicenter, randomized clinical trial was conducted to determine the safety and efficacy of norethindrone acetate and ethinyl estradiol tablets on maintaining bone mineral density, protecting the endometrium, and to determine effects on lipids. A total of 1,265 women were enrolled and randomized to either placebo, 0.2 mg NA/1 mcg ethinyl estradiol (NA/EE 0.2 /1), 0.5 mg NA/2.5 mcg EE (NA/EE 0.5 /2.5), norethindrone acetate and ethinyl estradiol tablets 1/5 and 1 mg NA/10 mcg EE (NA/EE 1/10) or matching unopposed EE doses (1, 2.5, 5, or 10 mcg) for a total of 9 treatment groups. All participants received 1000 mg of calcium supplementation daily. Of the 1,265 women randomized to the various treatment arms of this study, 137 were randomized to placebo, 146 to norethindrone acetate and ethinyl estradiol tablets 1/5, 136 to NA/EE 0.5/2.5 and 141 to EE 5 mcg and 137 to EE 2.5 mcg. Of these, 134 placebo, 143 norethindrone acetate and ethinyl estradiol tablets 1/5, 136 NA/EE 0.5/2.5, 139 EE 5 mcg and 137 EE 2.5 mcg had a baseline endometrial result. Baseline biopsies were classified as normal (in approximately 95 percent of subjects), or insufficient tissue (in approximately 5 percent of subjects). Follow-up biopsies were obtained in approximately 70 to 80 percent of patients in each arm after 12 and 24 months of therapy. Results for norethindrone acetate and ethinyl estradiol tablets 1/5 and appropriate comparators are shown in Table 5.

Table 5. Endometrial Biopsy Results After 12 and 24 Months of Treatment (CHART Study, 376-359)

Endometrial Status | Placebo | Norethindrone Acetate and Ethinyl Estradiol Tablets |  | EE Alone
 |  | 0.5/2.5 | 1/5 | 2.5 mcg | 5 mcg
Number of Patients Biopsied at Baseline | N = 134 | N = 136 | N = 143 | N = 137 | N = 139
MONTH 12 (Percent Patients)
Patients Biopsied (percent) | 113 (84) | 103 (74) | 110 (77) | 100 (73) | 114 (82)
Insufficient Tissue | 30 | 34 | 45 | 20 | 20
Atrophic Tissue | 60 | 41 | 41 | 15 | 2
Proliferative Tissue | 23 | 28 | 24 | 65 | 91
Endometrial Hyperplasia * | 0 | 0 | 0 | 0 | 1
MONTH 24 (Percent Patients)
Patients Biopsied (percent) | 94 (70) | 99 (73) | 102 (71) | 89 (65) | 107 (77)
Insufficient Tissue | 35 | 42 | 37 | 23 | 17
Atrophic Tissue | 38 | 30 | 33 | 6 | 2
Proliferative Tissue | 20 | 27 | 32 | 60 | 86
Endometrial Hyperplasia * | 1 | 0 | 0 | 0 | 2

*All patients with endometrial hyperplasia were carried forward for all time points.

14.3 Effects on Uterine Bleeding or Spotting in Postmenopausal Women

The cumulative incidence of amenorrhea, defined as no bleeding or spotting obtained from participant recall, was evaluated over 12 months for norethindrone acetate and ethinyl estradiol tablets 1/5 and placebo arms. Results are shown in Figure 2.

Figure 2. Participants with Cumulative Amenorrhea Over Time: Intent-to-Treat Population, Last Observation Carried Forward

14.4 Effect on Bone Mineral Density in Postmenopausal Women

In the 2 year study, trabecular BMD was assessed at lumbar spine using quantitative computed tomography. A total of 419 postmenopausal primarily Caucasian women, 40 to 64 years of age, with intact uteri and non-osteoporotic bone mineral densities were randomized (1:1:1) to norethindrone acetate and ethinyl estradiol tablets 1/5, NA/EE 0.5/2.5 or placebo. Approximately 75 percent of the women in each group completed the two-year study. All women received 1000 mg calcium in divided doses. Vitamin D was not supplemented.

As shown in Figure 3, women treated with norethindrone acetate and ethinyl estradiol tablets 1/5 had an average increase of 3.1 percent in lumbar spine BMD from baseline to Month 24. Women treated with placebo had average decreases of –6.3 percent in spinal BMD from baseline to Month 24. The differences in the changes from baseline to Month 24 in the norethindrone acetate and ethinyl estradiol tablets 1/5 group compared with the placebo group was statistically significant.

Figure 3. Mean Percent Change (+ SE) From Baseline in Volumetric Bone Mineral Density* at Lumbar Spine Measured by Quantitative Computed Tomography after 12 and 24 Months of Treatment (Intent-to-Treat Population)

*It should be noted that when measured by QCT, BMD gains and losses are greater than when measured by dual X-ray absorptiometry (DXA). Therefore, the differences in the changes in BMD between the placebo and active drug treated groups will be larger when measured by QCT compared with DXA. Changes in BMD measured by DXA should not be compared with changes in BMD measured by QCT.

14.5 Women's Health Initiative Studies

The WHI enrolled approximately 27,000 predominantly healthy postmenopausal women in two substudies to assess the risks and benefits of daily oral CE (0.625 mg)-alone or in combination with MPA (2.5 mg) compared to placebo in the prevention of certain chronic diseases. The primary endpoint was the incidence of CHD (defined as nonfatal MI, silent MI and CHD death), with invasive breast cancer as the primary adverse outcome. A “global index” included the earliest occurrence of CHD, invasive breast cancer, stroke, PE, endometrial cancer (only in the CE plus MPA substudy), colorectal cancer, hip fracture, or death due to other cause. The study did not evaluate the effects of CE plus MPA or CE-alone on menopausal symptoms.

WHI Estrogen Plus Progestin Substudy

The WHI estrogen plus progestin substudy was stopped early. According to the predefined stopping rule, after an average follow-up of 5.6 years of treatment, the increased risk of invasive breast cancer and cardiovascular events exceeded the specified benefits included in the “global index”. The absolute excess risk of events included in the “global index” was 19 per 10,000 women-years.

For those outcomes included in the WHI “global index” that reached statistical significance after 5.6 years of follow-up, the absolute excess risks per 10,000 women-years in the group treated with CE plus MPA were 7 more CHD events, 8 more strokes, 10 more PEs, and 8 more invasive breast cancers, while the absolute risk reductions per 10,000 women-years were 6 fewer colorectal cancers and 5 fewer hip fractures.

Results of the CE plus MPA substudy, which included 16,608 women (average 63 years of age, range 50 to 79; 83.9 percent White, 6.8 percent Black, 5.4 percent Hispanic, 3.9 percent Other) are presented in Table 6. These results reflect centrally adjudicated data after an average follow-up of 5.6 years.

Table 6. Relative and Absolute Risk Seen in the Estrogen Plus Progestin Substudy of WHI at an Average of 5.6 Years ¶ #Ϸ

Event | Relative Risk CE/MPA vs. Placebo (95 percent nCIß) | CE/MPA; n = 8,506 | Placebo n = 8,102
 |  | Absolute Risk per 10,000 Women-Years
CHD events | 1.23 (0.99 to 1.53) | 41 | 34
Non-fatal MI | 1.28 (1 to 1.63) | 31 | 25
CHD death | 1.10 (0.7 to 1.75) | 8 | 8
All strokes | 1.31 (1.03 to 1.68) | 33 | 25
Ischemic stroke | 1.44 (1.09 to 1.9) | 26 | 18
Deep vein thrombosis à | 1.95 (1.43 to 2.67) | 26 | 13
Pulmonary embolism | 2.13 (1.45 to 3.11) | 18 | 8
Invasive breast cancer ẻ | 1.24 (1.01 to 1.54) | 41 | 33
Colorectal cancer | 0.61 (0.42 to 0.87) | 10 | 16
Endometrial cancer à | 0.81 (0.48 to 1.36) | 6 | 7
Cervical cancer à | 1.44 (0.47 to 4.42) | 2 | 1
Hip fracture | 0.67 (0.47 to 0.96) | 11 | 16
Vertebral fractures à | 0.65 (0.46 to 0.92) | 11 | 17
Lower arm/wrist fractures à | 0.71 (0.59 to 0.85) | 44 | 62
Total fractures à | 0.76 (0.69 to 0.83) | 152 | 199
Overall Mortality ß ð | 1 (0.83 to 1.19) | 52 | 52
Global Index ø | 1.13 (1.02 to 1.25) | 184 | 165

¶ Adapted from numerous WHI publications. WHI publications can be viewed at www.nhlbi.nih.gov/whi.

#Ϸ Results are based on centrally adjudicated data.

ß Nominal confidence intervals unadjusted for multiple looks and multiple comparisons.

à Not included in "global index".

ẻ Includes metastic and non-metastic breast cancer with the exception of in situ cancer.

ð All deaths, except from breast or colorectal cancer, definite or probable CHD, PE or cerebrovascular disease.

ø A subset of the events was combined in a "global index" defined as the earliest occurrence of CHD events, invasive breast cancer, stroke, pulmonary embolism, colorectal cancer, hip fracture, or death due to other causes.

Timing of the initiation of estrogen plus progestin therapy relative to the start of menopause may affect the overall risk benefit profile. The WHI estrogen plus progestin substudy stratified by age showed in women 50 to 59 years of age, a non-significant trend toward reduced risk for overall mortality [(hazard ratio (HR) 0.69 (95 percent CI, 0.44 to 1.07)].

WHI Estrogen-Alone Substudy

The WHI estrogen-alone substudy was also stopped early because an increased risk of stroke was observed, and it was deemed that no further information would be obtained regarding the risks and benefits of estrogen-alone in predetermined primary endpoints.

Results of the estrogen-alone substudy, which included 10,739 women (average 63 years of age, range 50 to 79; 75.3 percent White, 15.1 percent Black, 6.1 percent Hispanic, 3.6 percent Other), after an average follow-up of 7.1 years, are presented in Table 7.

Table 7. Relative and Absolute Risk Seen in the Estrogen-Alone Substudy of WHI¥

Event | Relative Risk CE vs. Placebo (95 percent nCICE | CE N = 5,310 | Placebo n = 5,429
 |  | Absolute Risk per 10,000 Women-Years
CHD eventsce | 0.95 (0.78 to 1.16) | 54 | 57
Non-fatal MIce | 0.91 (0.73 to1.14) | 40 | 42
CHD deathce | 1.01 (0.71 to1.43) | 16 | 16
All strokesce | 1.33 (1.05 to 1.68) | 45 | 33
Ischemic strokece | 1.55 (1.19 to 2.01) | 38 | 25
Deep vein thrombosisce Đ | 1.47 (1.06 to 2.06) | 23 | 15
Pulmonary embolismce | 1.37 (0.90 to 2.07) | 14 | 10
Invasive breast cancerce | 0.80 (0.62 to 1.04) | 28 | 34
Colorectal cancer* | 1.08 (0.75 to 1.55) | 17 | 16
Hip fracturece | 0.65 (0.45 to 0.94) | 12 | 19
Vertebral fracturesce Đ | 0.64 (0.44 to 0.93) | 11 | 18
Lower arm/wrist fractures ce Đ | 0.58 (0.47 to 0.72) | 35 | 59
Total fractures ce Đ | 0.71 (0.64 to 0.8) | 144 | 197
Deaths due to other causes* † | 1.08 (0.88 to 1.32) | 53 | 50
Overall Mortality ce Đ | 1.04 (0.88 to 1.22) | 79 | 75
Global Index‡ | 1.02(0.92 to 1.13) | 206 | 201

¥ Adapted from numerous WHI publications. WHI publications can be viewed at www.nblbi.nih.gov/whi.

CE Nominal confidence intervals unadjusted for multiple looks and multiple comparisons.

ce Results are based on centrally adjudicated data for an average follow-up of 7.1 years.

Đ Not included in "global index".

* Results are based on an average follow-up of 6.8 years.

† All deaths, except from breast or colorectal cancer, definite or probable CHD, PE or cerebrovascular disease.

‡ A subset of the events was combined in a "global index" defined as the earliest occurrence of CHD events, invasive breast cancer, stroke, pulmonary embolism, colorectal cancer, hip fracture, or death due to other causes.

For those outcomes included in the WHI “global index” that reached statistical significance, the absolute excess risk per 10,000 women-years in the group treated with CE-alone were 12 more strokes, while the absolute risk reduction per 10,000 women-years was 7 fewer hip fractures.^9 The absolute excess risk of events included in the “global index” was a non- significant 5 events per 10,000 women-years. There was no difference between the groups in terms of all-cause mortality.

No overall difference for primary CHD events (nonfatal MI, silent MI and CHD death) and invasive breast cancer incidence in women receiving CE-alone compared with placebo was reported in final centrally adjudicated results from the estrogen-alone substudy, after an average follow-up of 7.1 years (see Table 7).

Centrally adjudicated results for stroke events from the estrogen-alone substudy, after an average follow-up of 7.1 years, reported no significant difference in distribution of stroke subtype or severity, including fatal strokes, in women receiving CE-alone compared to placebo. Estrogen-alone therapy increased the risk of ischemic stroke, and this excess was present in all subgroups of women examined^10 (see Table 7).

Timing of the initiation of estrogen-alone therapy relative to the start of menopause may affect the overall risk benefit profile. The WHI estrogen-alone substudy stratified by age, showed in women 50 to 59 years of age a non-significant trend toward reduced risk for CHD [HR 0.63 (95 percent CI, 0.36 to 1.09)] and overall mortality [HR 0.71 (95 percent CI, 0.46 to 1.11)].

14.6 Women's Health Initiative Memory Study

The WHIMS estrogen plus progestin ancillary study of WHI enrolled 4,532 predominantly healthy postmenopausal women 65 years of age and older (47 percent were 65 to 69 years of age, 35 percent were 70 to 74 years of age, and 18 percent were 75 years of age and older) to evaluate the effects of CE (0.625 mg) plus MPA (2.5 mg) on the incidence of probable dementia (primary outcome) compared to placebo.

After an average follow-up of 4 years, the relative risk of probable dementia for CE plus MPA versus placebo was 2.05 (95 percent CI, 1.21 to 3.48). The absolute risk of probable dementia for CE plus MPA versus placebo was 45 versus 22 per 10,000 women-years. Probable dementia as defined in this study included Alzheimer’s disease (AD), vascular dementia (VaD) and mixed types (having features of both AD and VaD). The most common classification of probable dementia in the treatment group and the placebo group was AD. Since the ancillary study was conducted in women 65 to 79 years of age, it is unknown whether these findings apply to younger postmenopausal women [see Warnings and Precautions (5.3), and Use in Specific Populations (8.5)].

The WHIMS estrogen-alone ancillary study of WHI enrolled 2,947 predominantly healthy hysterectomized postmenopausal women 65 to 79 years of age and older (45 percent were 65 to 69 years of age; 36 percent were 70 to 74 years of age; 19 percent were 75 years of age and older) to evaluate the effects of daily CE (0.625 mg)-alone on the incidence of probable dementia (primary outcome) compared to placebo.

After an average follow-up of 5.2 years, the relative risk of probable dementia for CE-alone versus placebo was 1.49 (95 percent CI, 0.83 to 2.66). The absolute risk of probable dementia for CE-alone versus placebo was 37 versus 25 cases per 10,000 women-years. Probable dementia as defined in this study included AD, VaD and mixed types (having features of both AD and VaD). The most common classification of probable dementia in the treatment group and the placebo group was AD. Since the ancillary study was conducted in women 65 to 79 years of age, it is unknown whether these findings apply to younger postmenopausal women [see Warnings and Precautions (5.3), and Use in Specific Populations (8.5)].

When data from the two populations were pooled as planned in the WHIMS protocol, the reported overall relative risk for probable dementia was 1.76 (95 percent CI, 1.19 to 2.6). Differences between groups became apparent in the first year of treatment. It is unknown whether these findings apply to younger postmenopausal women [see Warnings and Precautions (5.3), and Use in Specific Populations (8.5)].

15 REFERENCES

1. Rossouw JE, et al. Postmenopausal Hormone Therapy and Risk of Cardiovascular Disease by Age and Years Since Menopause. JAMA. 2007;297:1465-1477.

2. Hsia J, et al. Conjugated Equine Estrogens and Coronary Heart Disease. Arch Int Med. 2006;166:357-365.

3. Cushman M, et al. Estrogen Plus Progestin and Risk of Venous Thrombosis. JAMA. 2004;292:1573-1580.

4. Curb JD, et al. Venous Thrombosis and Conjugated Equine Estrogen in Women Without a Uterus. Arch Int Med. 2006;166:772-780.

5. Chlebowski RT, et al. Influence of Estrogen Plus Progestin on Breast Cancer and Mammography in Healthy Postmenopausal Women. JAMA. 2003;289:3234-3253.

6. Stefanick ML, et al. Effects of Conjugated Equine Estrogens on Breast Cancer and Mammography Screening in Postmenopausal Women With Hysterectomy. JAMA. 2006;295:1647-1657.

7. Anderson GL, et al. Effects of Estrogen Plus Progestin on Gynecologic Cancers and Associated Diagnostic Procedures. JAMA. 2003;290:1739-1748.

8. Shumaker SA, et al. Conjugated Equine Estrogens and Incidence of Probable Dementia and Mild Cognitive Impairment in Postmenopausal Women. JAMA. 2004;291:2947-2958.

9. Jackson RD, et al. Effects of Conjugated Equine Estrogen on Risk of Fractures and BMD in Postmenopausal Women With Hysterectomy: Results From the Women’s Health Initiative Randomized Trial. J Bone Miner Res. 2006;21:817-828.

10. Hendrix SL, et al. Effects of Conjugated Equine Estrogen on Stroke in the Women’s Health Initiative. Circulation. 2006;113:2425-2434.

16 HOW SUPPLIED/STORAGE AND HANDLING

16.1 How Supplied

Norethindrone Acetate and Ethinyl Estradiol Tablets, USP are available in the following strengths and package sizes:

Norethindrone Acetate and Ethinyl Estradiol Tablets, USP 0.5 mg/2.5 mcg, are light pink to pink, round, flat-faced, beveled edge, uncoated, tablets debossed with “D5” on one side and plain on the other side. Each tablet contains 0.5 mg norethindrone acetate, USP and 2.5 mcg ethinyl estradiol, USP and are available as:

NDC 68462-656-90 Bottle of 90 Tablets

NDC 68462-656-29 1 carton containing 3 individual foil pouches (68462-656-84). Each pouch contains 1 blister of 28 tablets (68462-656-84)

Norethindrone Acetate and Ethinyl Estradiol Tablets, USP 1 mg/5 mcg are white to off-white, round, flat-faced, beveled edge, uncoated tablets debossed with “D6” on one side plain on the other side. Each tablet contains 1 mg norethindrone acetate, USP and 5 mcg ethinyl estradiol, USP and are available as:

NDC 68462-657-90 Bottle of 90 Tablets

NDC 68462-657-29 1 carton containing 3 individual foil pouches (68462-657-84). Each pouch contains 1 blister of 28 tablets (68462-657-84).

16.2 Storage and Handling

Store at 20°C to 25°C (68°F to 77°F); excursions permitted to 15°C to 30°C (59°F to 86°F) [See USP Controlled Room Temperature].

Keep norethindrone acetate and ethinyl estradiol tablets out of the reach of children.

17 PATIENT COUNSELING INFORMATION

Advise women to read the FDA-approved patient labeling (Patient Information)

Vaginal Bleeding

Inform postmenopausal women to report any vaginal bleeding to their healthcare provider as soon as possible [see Warnings and Precautions (5.2)].

Possible Serious Adverse Reactions with Estrogen Plus Progestogen Therapy

Inform postmenopausal women of possible serious adverse reactions of estrogen plus progestogen therapy including Cardiovascular Disorders, Malignant Neoplasms, and Probable Dementia [see Warnings and Precautions (5.1, 5.2, 5.3)].

Possible Common Adverse Reactions with Estrogen Plus Progestogen Therapy

Inform postmenopausal women of possible less serious but common adverse reactions of estrogen plus progetogen therapy such as headache, breast pain and tenderness, nausea and vomiting.

Distributed by:

Glenmark Pharmaceuticals Inc., USA
Elmwood Park, NJ 07407

Questions? 1 (888) 721-7115
www.glenmarkpharma-us.com

May 2025

PATIENT INFORMATION

Norethindrone Acetate and Ethinyl Estradiol (nor-eth-IN-drone ASS-uh-TATE and ETH in il es tra DYE ole) Tablets, USP

0.5 mg/2.5 mcg and 1 mg/5 mcg

Read this Patient Information before you start using norethindrone acetate and ethinyl estradiol tablets and each time you get a refill. There may be new information. This information does not take the place of talking to your healthcare provider about your menopausal symptoms or your treatment.

What is the most important information I should know about norethindrone acetate and ethinyl estradiol tablets (a combination of estrogen and progestogen)?

- Do not use estrogens with or without progestogens to prevent heart disease, heart attacks, strokes or dementia (decline of brain function).
- Using estrogens with progestogens may increase your chances of getting heart attack, strokes, breast cancer, or blood clots.
- Using estrogens with progestogens may increase your chance of getting dementia, based on a study of women 65 years of age and older.
- Using estrogen-alone may increase your chance of getting cancer of the uterus (womb).
- Do not use estrogen-alone to prevent heart disease, heart attacks, strokes or dementia (decline of brain function).
- Using estrogen-alone may increase your chances of getting strokes or blood clots.
- Using estrogen-alone may increase your chance of getting dementia, based on a study of women 65 years of age and older.
- Only one estrogen with progestogen product and dose have been shown to increase your chances of getting heart attacks, strokes, breast cancer, blood clots, and dementia. Only one estrogen-alone product and dose have been shown to increase your chances of getting strokes, blood clots, and dementia. Because other products and doses have not been studied in the same way, it is not known how the use of norethindrone acetate and ethinyl estradiol tablets will affect your chances of these conditions. You and your healthcare provider should talk regularly about whether you still need treatment with norethindrone acetate and ethinyl estradiol tablets.

What are norethindrone acetate and ethinyl estradiol tablets?

Norethindrone acetate and ethinyl estradiol tablets are a prescription medicine that contains two kinds of hormones, an estrogen and a progestogen.

What are norethindrone acetate and ethinyl estradiol tablets used for?

Norethindrone acetate and ethinyl estradiol tablets are used after menopause to:

- Reduce moderate to severe hot flushes
Estrogens are hormones made by a woman’s ovaries. The ovaries normally stop making estrogens when a woman is between 45 and 55 years old. This drop in body estrogen levels causes the “change of life” or menopause, the end of monthly menstrual periods. Sometimes both ovaries are removed during an operation before natural menopause takes place. The sudden drop in estrogen levels causes “surgical menopause”.
When estrogen levels begin dropping, some women get very uncomfortable symptoms, such as feelings of warmth in the face, neck, and chest, or sudden intense episodes of heat and sweating (“hot flashes” or “hot flushes”). In some women the symptoms are mild, and they will not need to take estrogens. In other women, symptoms can be more severe.
- Help reduce your chances of getting osteoporosis (thin weak bones)
If you use norethindrone acetate and ethinyl estradiol tablets only to prevent osteoporosis from menopause, talk with your healthcare provider about whether a different treatment or medicine without estrogens might be better for you. You and your healthcare provider should talk regularly about whether you still need treatment with norethindrone acetate and ethinyl estradiol tablets.

Who should not use norethindrone acetate and ethinyl estradiol tablets?

Do not use norethindrone acetate and ethinyl estradiol tablets if you have had your uterus (womb) removed (hysterectomy).

Norethindrone acetate and ethinyl estradiol tablets contain a progestogen to decrease the chance of getting cancer of the uterus (womb). If you do not have a uterus, you do not need a progestogen and you should not take norethindrone acetate and ethinyl estradiol tablets.

Do not start using norethindrone acetate and ethinyl estradiol tablets if you:

- have any unusual vaginal bleeding.
Vaginal bleeding after menopause may be a warning sign of cancer of the uterus (womb). Your healthcare provider should check any unusual vaginal bleeding to find out the cause.
- have been diagnosed with a bleeding disorder.
- currently have or have had certain cancers.
Estrogens may increase the chance of getting certain types of cancers, including cancer of the breast or uterus (womb). If you have or have had cancer, talk with your healthcare provider about whether you should take norethindrone acetate and ethinyl estradiol tablets.
- had a stroke or heart attack
- currently have or have had blood clots
- currently have or have had liver problems
- are allergic to norethindrone acetate and ethinyl estradiol tablets or any of its ingredients.
See the list of ingredients in norethindrone acetate and ethinyl estradiol tablets at the end of this leaflet.

Before you use norethindrone acetate and ethinyl estradiol tablets, tell your healthcare provider about all of your medical conditions, including if you:

- have any unusual vaginal bleeding
Vaginal bleeding after menopause may be a warning sign of cancer of the uterus (womb). Your healthcare provider should check any unusual vaginal bleeding to find out the cause.
- have any other medical conditions that may become worse while you are using norethindrone acetate and ethinyl estradiol tablets.
Your healthcare provider may need to check you more carefully if you have certain conditions, such as asthma (wheezing), epilepsy (seizures), diabetes, migraine, endometriosis, lupus, angioedema (swelling of face and tongue), or problems with your heart, liver, thyroid, kidneys, or have high calcium levels in your blood.
- are going to have surgery or will be on bed rest
Your healthcare provider will let you know if you need to stop using norethindrone acetate and ethinyl estradiol tablets.
- are pregnant or think you may be pregnant.
Norethindrone acetate and ethinyl estradiol tablets is not for pregnant women.
- are breastfeeding
The hormones in norethindrone acetate and ethinyl estradiol tablets can pass into your breast milk.

Tell your healthcare provider about all the medicines you take, including prescription and over-the-counter medicines, vitamins, and herbal supplements. Some medicines may affect how norethindrone acetate and ethinyl estradiol tablets works. Some other medicines and food products may increase or decrease the concentrations of the hormones in norethindrone acetate and ethinyl estradiol tablets in the blood. Norethindrone acetate and ethinyl estradiol tablets may also affect how your other medicines work. Keep a list of your medicines and show it to your healthcare provider and pharmacist when you get a new medicine.

How should I use norethindrone acetate and ethinyl estradiol tablets?

- Take norethindrone acetate and ethinyl estradiol tablets exactly as your healthcare provider tells you to take it.
- Take 1 norethindrone acetate and ethinyl estradiol tablet at the same time each day.
- You and your healthcare provider should talk regularly (every 3 to 6 months) about the dose you are taking and whether or not you still need treatment with norethindrone acetate and ethinyl estradiol tablets.

What are the possible side effects of norethindrone acetate and ethinyl estradiol tablets?

Side effects are grouped by how serious they are and how often they happen when you are treated.

Serious, but less common side effects include:

- Heart attack
- Stroke
- Blood clots
- Breast cancer
- Cancer of the lining of the uterus (womb)
- Cancer of the ovary
- Dementia
- Gallbladder disease
- High or low blood calcium levels
- Changes in vision
- High blood pressure
- High levels of fat in your blood
- Liver problems
- Changes in your thyroid hormone levels
- Swelling or fluid retention
- Cancer changes of endometriosis
- Enlargement of benign tumors of the uterus (“fibroids”)
- Worsening swelling of face or tongue (angioedema) in women who have a history of angioedema
- Changes in laboratory test results such as bleeding time and high blood sugar levels

Call your healthcare provider right away if you get any of the following warning signs or any other unusual symptoms that concern you:

- new breast lumps
- unusual vaginal bleeding
- changes in vision or speech
- sudden new severe headaches
- severe pains in your chest or legs with or without shortness of breath, weakness and fatigue

Common side effects of norethindrone acetate and ethinyl estradiol tablets include:

- headache
- breast pain
- irregular vaginal bleeding or spotting
- stomach or abdominal cramps, bloating
- hair loss
- fluid retention
- vaginal yeast infection

These are not all the possible side effects of norethindrone acetate and ethinyl estradiol tablets. For more information, ask your healthcare provider or pharmacist. Tell your healthcare provider if you have any side effects that bother you or does not go away.

You may report side effects to Glenmark Pharmaceuticals Inc., USA at 1 (888) 721-7115 or FDA at 1-800-FDA-1088.

What can I do to lower my chances of a serious side effect with norethindrone acetate and ethinyl estradiol tablets?

- Talk with your healthcare provider regularly about whether you should continue using norethindrone acetate and ethinyl estradiol tablets.
- If you have a uterus, talk with your healthcare provider about whether norethindrone acetate and ethinyl estradiol tablet is right for you.
- In general, the addition of a progestogen is recommended for a woman with a uterus to reduce the chance of getting cancer of the uterus (womb).
- See your healthcare provider right away if you get vaginal bleeding while using norethindrone acetate and ethinyl estradiol tablets.
- Have a pelvic exam, breast exam and mammogram (breast x-ray) every year unless your healthcare provider tells you something else.
- If members of your family have had breast cancer or if you have ever had breast lumps or an abnormal mammogram (breast x-ray), you may need to have breast exams more often.
- If you have high blood pressure, high cholesterol (fat in the blood), diabetes, are overweight, or use tobacco, you may have a higher chance for getting heart disease.

Ask your healthcare provider for ways to lower your chances of getting heart disease.

How should I store norethindrone acetate and ethinyl estradiol tablets?

Store norethindrone acetate and ethinyl estradiol tablets at 20°C to 25°C (68°F to 77°F); excursions permitted to 15°C to 30°C (59°F to 86°F).

Keep norethindrone acetate and ethinyl estradiol tablets out of the reach of children.

General information about the safe and effective use of norethindrone acetate and ethinyl estradiol tablets.

Medicines are sometimes prescribed for conditions that are not mentioned in patient information leaflets. Do not use norethindrone acetate and ethinyl estradiol tablets for conditions for which it was not prescribed. Do not give norethindrone acetate and ethinyl estradiol tablets to other people, even if they have the same symptoms you have. It may harm them.

You can ask your pharmacist or healthcare provider for information about norethindrone acetate and ethinyl estradiol tablets that is written for health professionals.

For more information about norethindrone acetate and ethinyl estradiol tablets, call Glenmark Pharmaceuticals Inc., USA at 1 (888) 721-7115.

What are the ingredients in norethindrone acetate and ethinyl estradiol tablets?

Active Ingredients: norethindrone acetate, USP and ethinyl estradiol, USP

Inactive Ingredients: calcium stearate, cornstarch, lactose monohydrate, microcrystalline cellulose, povidone and vitamin E and talc. The 0.5 mg/2.5 mcg light pink to pink tablets also contain D&C red no. 30.

This Patient Information has been approved by the U.S Food and Drug Administration.

Distributed by:

Glenmark Pharmaceuticals Inc., USA
Elmwood Park, NJ 07407

Questions? 1 (888) 721-7115

www.glenmarkpharma-us.com

May 2025